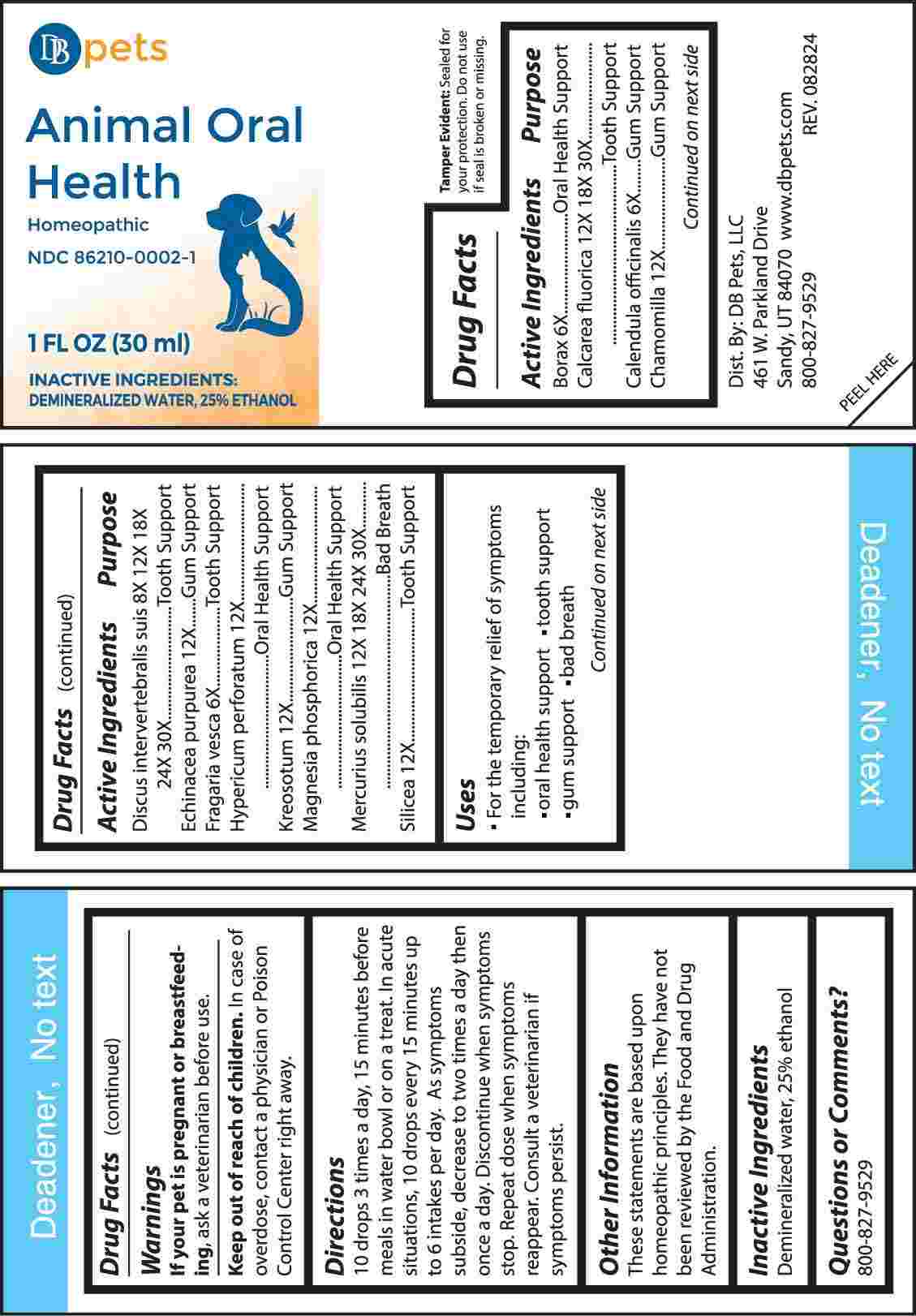 DRUG LABEL: Animal Oral Health
NDC: 86210-0002 | Form: LIQUID
Manufacturer: DB Pets LLC
Category: homeopathic | Type: OTC ANIMAL DRUG LABEL
Date: 20241001

ACTIVE INGREDIENTS: SODIUM BORATE 6 [hp_X]/1 mL; CALCIUM FLUORIDE 12 [hp_X]/1 mL; CALENDULA OFFICINALIS FLOWERING TOP 6 [hp_X]/1 mL; MATRICARIA CHAMOMILLA WHOLE 12 [hp_X]/1 mL; SUS SCROFA INTERVERTEBRAL DISC 8 [hp_X]/1 mL; ECHINACEA PURPUREA WHOLE 12 [hp_X]/1 mL; FRAGARIA VESCA FRUIT 6 [hp_X]/1 mL; HYPERICUM PERFORATUM WHOLE 12 [hp_X]/1 mL; WOOD CREOSOTE 12 [hp_X]/1 mL; MAGNESIUM PHOSPHATE, DIBASIC TRIHYDRATE 12 [hp_X]/1 mL; MERCURIUS SOLUBILIS 12 [hp_X]/1 mL; SILICON DIOXIDE 12 [hp_X]/1 mL
INACTIVE INGREDIENTS: WATER; ALCOHOL

DRUG FACTS:

ACTIVE INGREDIENTS:

Borax 6X, Calcarea Fluorica 12X, 18X, 30X, Calendula Officinalis 6X, Chamomilla 12X, Discus Intervertebralis Suis 8X, 12X, 18X, 24X, 30X, , Echinacea Purpurea 12X, Fragaria Vesca 6X, Hypericum Perforatum 12X, Kreosotum 12X, Magnesia Phosphorica 12X, Mercurius Solubilis 12X, 18X, 24X, 30X, Silicea 12X.

PURPOSE:

Borax – Oral Health Support, Calcarea Fluorica – Tooth Support, Calendula Officinalis – Gum Support, Chamomilla – Gum Support, Discus Intervertebralis Suis – Tooth Support, Echinacea Purpurea – Gum Support, Fragaria Vesca – Tooth Support, Hypericum Perforatum – Oral Health Support, Kreosotum – Gum Support, Magnesia Phosphorica – Oral Health Support, Mercurius Solubilis – Bad Breath, Silicea – Tooth Support

USES:

• For the temporary relief of symptoms including:

•oral health support •tooth support •gum support •bad breath

These statements are based upon homeopathic principles. They have not been reviewed by the Food and Drug Administration.

WARNINGS:

If your pet is pregnant or breastfeeding, ask a veterinarian before use.

Keep out of reach of children. In case of overdose, contact a physician or Poison Control Center right away.

Tamper Evident: Sealed for your protection. Do not use if seal is broken or missing.

KEEP OUT OF THE REACH OF CHILDREN:

In case of overdose, contact a physician or Poison Control Center right away.

DIRECTIONS:

10 drops 3 times a day, 15 minutes before meals in water bowl or on a treat. In acute situations, 10 drops every 15 minutes up to 6 intakes per day. As symptoms subside, decrease to two times a day then once a day. Discontinue when symptoms stop. Repeat dose when symptoms reappear. Consult a veterinarian if symptoms persist.

INACTIVE INGREDIENTS:

Demineralized water, 25% ethanol

QUESTIONS:

Dist. By: DB Pets, LLC

461 W. Parkland Drive

Sandy, UT 84070

www.dbpets.com

800-827-9529

PACKAGE LABEL DISPLAY:

DB pets

Animal Oral Health

Homeopathic

NDC 86210-0002-1

1 FL OZ (30 ml)